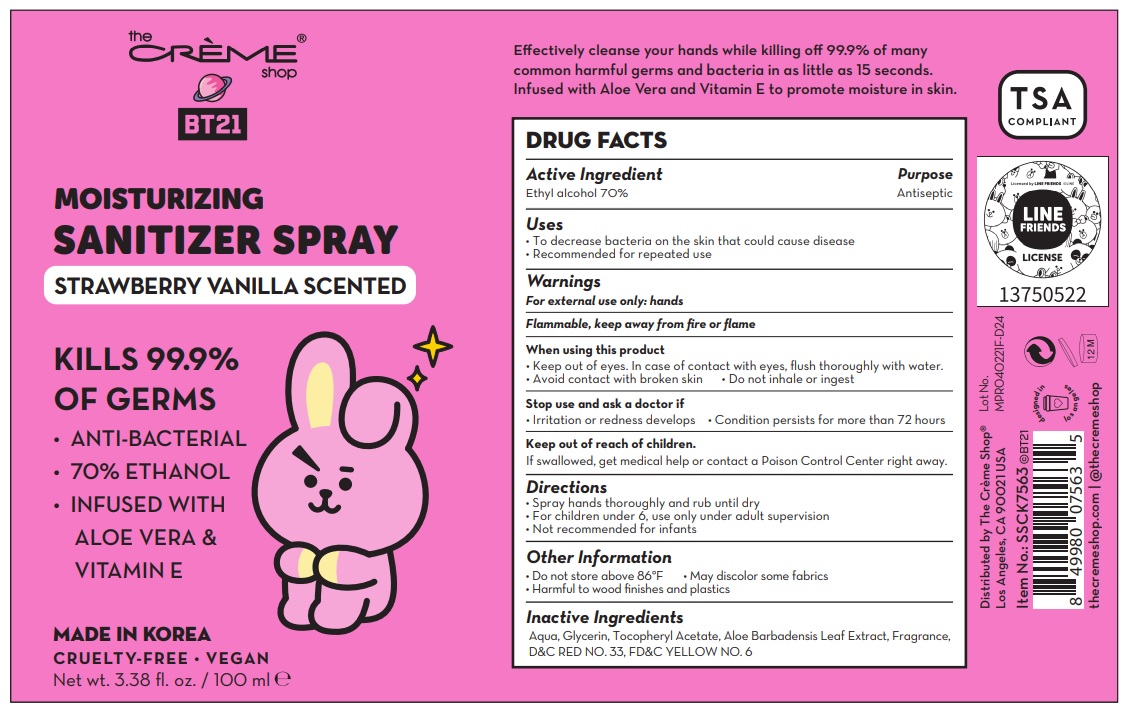 DRUG LABEL: The creme shop BT21 MOISTURIZING SANITIZERSpray STRAWBERRY VANILLA SCENTED
NDC: 81123-076 | Form: SPRAY
Manufacturer: The Creme Shop Inc
Category: otc | Type: HUMAN OTC DRUG LABEL
Date: 20210325

ACTIVE INGREDIENTS: ALCOHOL 70 mL/100 mL
INACTIVE INGREDIENTS: ALOE VERA LEAF; GLYCERIN; .ALPHA.-TOCOPHEROL ACETATE; WATER; D&C RED NO. 33; FD&C YELLOW NO. 6

81123-076-01
The creme shop BT21 MOISTURIZING SANITIZER SPRAY STRAWBERRY VANILLA SCENTED
Bottle+Spray

PACKAGE LABEL

Active ingredient

Ethyl alcohol 70 %

Purpose

Antiseptic

Other Information

Do not store above 86 °F

May discolor some fabrics

Harmful to wood finishes and plastics

Inactive ingredients

Aqua, Glycerin, Tocopheryl Acetate, Aloe Barbadensis Leaf Extract, Fragrance, D&C RED NO. 33, FD&C YELLOW NO. 6

Keep out of reach of children.

If swallowed, get medical help or contact a Poison Control Center right away.

When using this product

Keep out of eyes. In case of contact with eyes, flush thoroughly with water.

Avoid contact with broken skin.

Do not inhale or ingest.

Directions

Spray hands thoroughly and rub until dry

For children under 6, use only under adult supervision

Not recommended for infants

Warnings

For external use only: hands

Flammable, keep away from fire or flame.

Stop use and ask a doctor if

Irritation or redness develops

Conditions persists for more than 72 hours